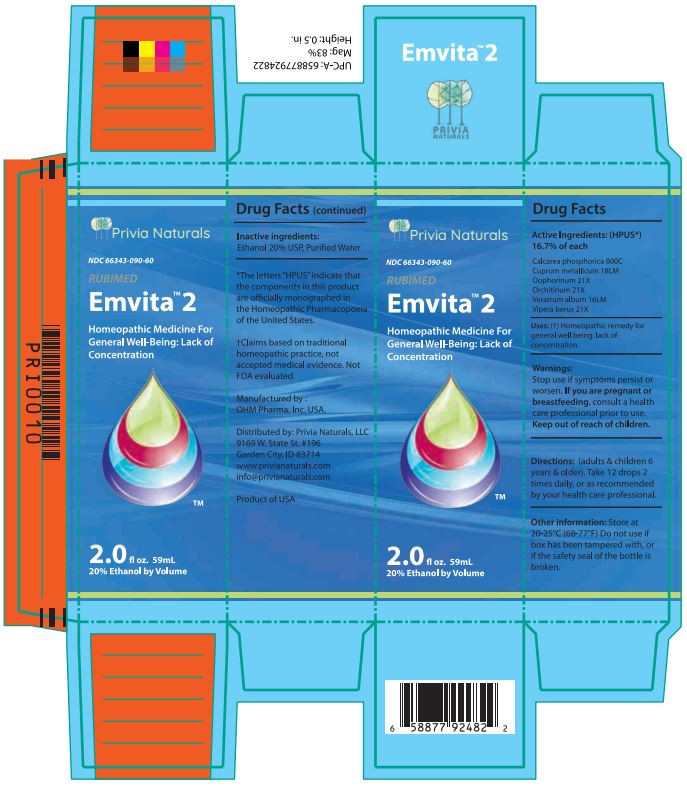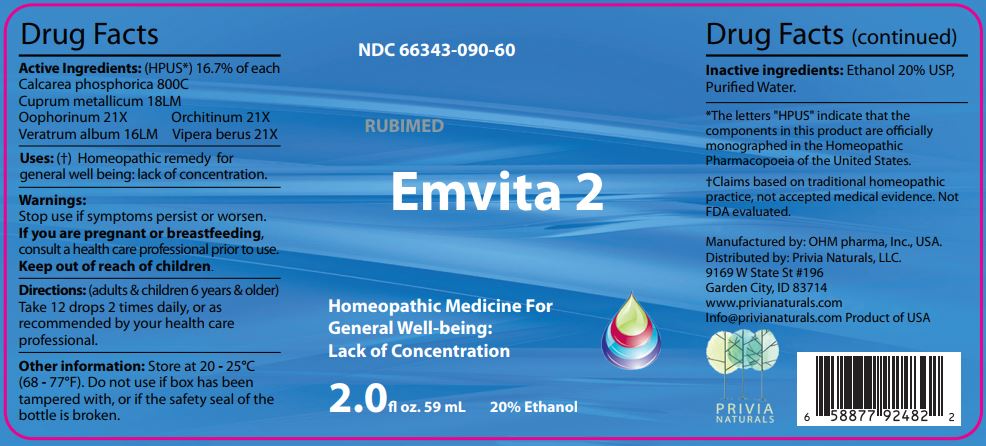 DRUG LABEL: Emvita 2
NDC: 66343-090 | Form: LIQUID
Manufacturer: RUBIMED AG
Category: homeopathic | Type: HUMAN OTC DRUG LABEL
Date: 20241029

ACTIVE INGREDIENTS: TRIBASIC CALCIUM PHOSPHATE 800 [hp_C]/60 mL; COPPER 18 [hp_M]/60 mL; SUS SCROFA OVARY 21 [hp_X]/60 mL; BOS TAURUS TESTICLE 21 [hp_X]/60 mL; VERATRUM ALBUM ROOT 16 [hp_M]/60 mL; VIPERA BERUS VENOM 21 [hp_X]/60 mL
INACTIVE INGREDIENTS: ALCOHOL; WATER

Emvita 2

ACTIVE INGREDIENT

Drug Facts Active Ingredients: (HPUS*) 16.7% of each

Calcarea phosphorica 800C
Cuprum metallicum 18LM
Oophorinum 21X Orchitinum 21X
Veratrum album 16LM Vipera berus 21X

*The letters "HPUS" indicate that the components in this product are officially monographed in the Homeopathic Pharmacopoeia of the United States. †Claims based on traditional homeopathic practice, not accepted medical evidence. Not FDA evaluated.

INDICATIONS AND USAGE

Uses: (†) Homeopathic remedy for lack of concentration.

Warnings:

Stop use if symptoms persist or worsen.

If you are pregnant or breastfeeding,consult a healthcare professional prior to use.

Keep out of reach of children.

DOSAGE AND ADMINISTRATION

Directions: (adults & children 6 years & older)

Take 12 drops 2 times daily, or as recommended by your health care professional.

Other information: Store at 20 - 25°C

(68 - 77°F.) Do not use if box has been

tampered with, or if the safety seal of the

bottle is broken.

Inactive ingredients:Ethanol 20% USP,

Purified Water.

QUESTIONS

Manufactured by: OHM pharma, Inc, USA.

Distributed by: Privia Naturals, LLC.

9169 W State St #196

Garden City, ID 83714

www.privianaturals.com

Info@privianaturals.com Product of USA.

PACKAGE LABEL

NDC 66343-090-60

RUBIMED

Emvita 2

Homeopathic Medicine For

Lack of Concentration

2.0 fl oz. 59mL 20% Ethanol

PURPOSE

Homeopathic Medicine For

Lack of Concentration